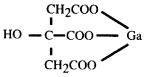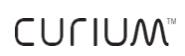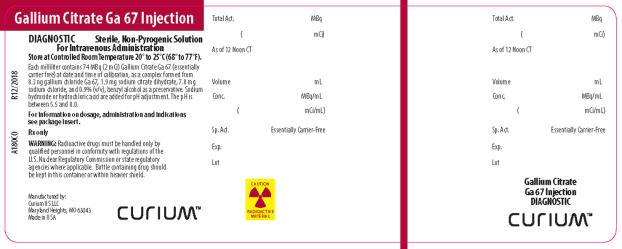 DRUG LABEL: GALLIUM CITRATE GA-67
NDC: 69945-180 | Form: INJECTION, SOLUTION
Manufacturer: Curium US LLC
Category: prescription | Type: HUMAN PRESCRIPTION DRUG LABEL
Date: 20250813

ACTIVE INGREDIENTS: GALLIUM CHLORIDE GA-67 2 mCi/1 mL
INACTIVE INGREDIENTS: TRISODIUM CITRATE DIHYDRATE; SODIUM CHLORIDE; BENZYL ALCOHOL; HYDROCHLORIC ACID; SODIUM HYDROXIDE

Gallium Citrate Ga 67 Injection

Rx only

Diagnostic–For Intravenous Use

DESCRIPTION

Gallium Citrate Ga 67 Injection is supplied in a 10 milliliter vial as an isotonic, sterile, non-pyrogenic solution. Each milliliter of the isotonic solution contains 74 megabecquerels (2 millicuries) of gallium Ga-67 on the calibration date as a complex formed from 8.3 nanograms gallium chloride Ga-67, 1.9 milligrams of sodium citrate dihydrate, 7.8 milligrams of sodium chloride and 0.9 percent benzyl alcohol (v/v) as a preservative. The pH is adjusted to between 5.5 to 8.0 with hydrochloric acid and/or sodium hydroxide solution.

Gallium Ga-67, with a half-life of 78.26 hours, is cyclotron produced by the proton irradiation of enriched zinc. At the time of calibration the drug contains no more than 0.02% gallium Ga-66 and no more than 0.2% zinc Zn-65. The concentration of each radionuclidic impurity changes with time. At expiration, the drug contains no more than 0.001% gallium Ga-66 and no more than 1.0% zinc Zn-65. No carrier has been added.

Gallium citrate has the following chemical structure:

Physical Characteristics

Gallium Ga-67 with a physical half-life of 78.26 hours^1decays by electron capture to stable zinc Zn-67. Photons that are useful for imaging studies are listed in Table 1.

Table 1. Principal Radiation Emission Data
Radiation | Mean Percent Per Disintegration | Energy (keV)
Gamma-2 Gamma-3 Gamma-4 Gamma-5 Gamma-6 Gamma-7 | 2.9 35.7 19.7 2.2 16.0 4.5 | 91.3 93.3 184.6 209.0 300.2 393.5

^1 Kocher, D.C., Radioactive Decay Data Tables, Health and Safety Research Division, National Technical Information Service, DOE/TIC-11026, pg. 80, 1981.

External Radiation

The specific gamma ray constant for gallium Ga-67 is 1.6 R/mCi-hour at 1 cm. The first half-value thickness of lead (Pb) is 0.066 cm. A range of values for the relative attenuation of the radiation emitted by this radionuclide that results from interposition of various thicknesses of lead is shown in Table 2. For example, the use of 1.2 cm of lead will decrease the radiation exposure by a factor of about 100.

Table 2. Radiation Attenuation by Lead Shielding
Shield Thickness (Pb), cm | Coefficient of Attenuation
0.066 0.41 1.2 2.5 4.8 | 0.5 10^-^1 10^-^2 10^-^3 10^-^4

To correct for physical decay of this radionuclide, the fractions that remain at selected time intervals after the time of calibration are shown in Table 3.

Table 3. Physical Decay Chart; Gallium Ga-67, Half-Life 78.26 Hours
Hours | Fraction Remaining | Hours | Fraction Remaining
0* 6 12 18 24 (1d) 30 36 42 48 (2d) 54 60 66 | 1.000 0.948 0.899 0.853 0.809 0.767 0.727 0.689 0.654 0.620 0.588 0.557 | 72 (3d) 78 84 90 96 (4d) 108 120 (5d) 132 144 (6d) 156 168 (7d) | 0.529 0.501 0.475 0.451 0.427 0.384 0.345 0.311 0.279 0.251 0.226

* Calibration Time

CLINICAL PHARMACOLOGY

Gallium Citrate Ga 67, with no carrier added, has been found to concentrate in certain viable primary and metastatic tumors as well as focal sites of infection. The mechanism of concentration is unknown, but investigational studies have shown that gallium Ga-67 accumulates in lysosomes and is bound to a soluble intracellular protein.

It has been reported in the scientific literature that following intravenous injection, the highest tissue concentration of gallium Ga-67 - other than tumors and sites of infection - is the renal cortex. After the first day, the maximum concentration shifts to bone and lymph nodes and after the first week, to liver and spleen. Gallium Ga-67 is excreted relatively slowly from the body. The average whole body retention is 65 percent after seven days, with 26 percent having been excreted in the urine and 9 percent in the stools.

INDICATIONS AND USAGE

Gallium Citrate Ga 67 Injection may be useful to demonstrate the presence and extent of Hodgkin's disease, lymphoma, and bronchogenic carcinoma. Positive gallium Ga-67 uptake in the absence of prior symptoms warrants follow-up as an indication of a potential disease state. Gallium Citrate Ga 67 Injection may be useful as an aid in detecting some acute inflammatory lesions.

CONTRAINDICATIONS

None.

WARNINGS

None known.

PRECAUTIONS

General

A thorough knowledge of the normal distribution of intravenously administered Gallium Citrate Ga 67 Injection is essential in order to accurately interpret pathologic states. The finding of an abnormal gallium Ga-67 concentration usually implies the existence of underlying pathology, but further diagnostic studies should be done to distinguish benign from malignant lesions. Gallium Citrate Ga 67 Injection is intended for use as an adjunct in the diagnosis of certain neoplasms as well as focal areas of infection. Certain pathologic conditions may yield up to 40 percent false negative gallium Ga-67 studies. Therefore, a negative study cannot be definitely interpreted as ruling out the presence of disease.

Lymphocytic lymphoma frequently does not accumulate gallium Ga-67 sufficiently for unequivocal imaging and the use of gallium with this histologic type of lymphoma is not recommended at this time.

Gallium Ga-67 localization cannot differentiate between tumor and acute inflammation, and other diagnostic studies must be added to define the underlying pathology.

As in the use of any radioactive material, care should be taken to minimize radiation exposure to the patient consistent with proper management and to ensure minimum radiation exposure to occupational workers.

The vial contents are sterile and non-pyrogenic. It is essential that the user follow the directions carefully and adhere to strict aseptic procedures.

Radiopharmaceuticals should be used only by physicians who are qualified by training and experience in the safe use and handling of radionuclides produced by nuclear reactor or particle accelerator and whose experience and training have been approved by the appropriate government agency authorized to license the use of radionuclides.

Carcinogenesis, Mutagenesis, Impairment of Fertility

No long-term animal studies have been performed to evaluate carcinogenic or mutagenic potential or whether this drug affects fertility in males or females.

Pregnancy

Animal reproductive studies have not been conducted with Gallium Citrate Ga 67. It is also not known whether Gallium Citrate Ga 67 can cause fetal harm when administered to a pregnant woman or can affect reproduction capacity. Gallium Citrate Ga 67 should be given to a pregnant woman only if clearly needed.

Ideally, examinations using radiopharmaceuticals, especially those elective in nature of women of childbearing capability, should be performed during the first few (approximately ten) days following the onset of menses.

Nursing Mothers

This drug is known to be excreted in human milk during lactation, therefore, formula feedings should be substituted for breast feedings.

Pediatric Use

Safety and effectiveness in pediatric patients below the age of 18 have not been established.

ADVERSE REACTIONS

Rare occurrences of allergic reactions, skin rash and nausea have been reported in association with Gallium Citrate Ga 67 use.

DOSAGE AND ADMINISTRATION

The recommended adult (70 kg) dose of Gallium Citrate Ga 67 Injection is 74 to 185 megabecquerels (2 to 5 millicuries). Gallium Citrate Ga 67 Injection is intended for intravenous administration only.

Approximately 10 percent of the administered dose is excreted in the feces during the first week after injection. Daily laxatives and/or enemas are recommended from the day of injection until the final images are obtained in order to cleanse the bowel of radioactive material and minimize the possibility of false positive studies.

Studies indicate the optimal tumor to background concentration ratios are often obtained 48 hours post injection. However, considerable biological variability may occur in individuals and acceptable images may be obtained as early as 6 hours and as late as 120 hours after injection.

The patient dose should be measured by a suitable radioactivity calibration system immediately prior to administration.

Parenteral drug products should be inspected visually for particulate matter and discoloration prior to administration. Do not use if contents are turbid.

Instructions for the handling of Gallium Citrate Ga 67:

1. Waterproof gloves should be used during the entire handling and administration procedure.
2. Using proper shielding, the vial containing the Gallium Citrate Ga 67 should be visually inspected to ensure that it is free of particulate matter and discoloration prior to use.
3. Maintain adequate shielding during the life of the product and use a sterile, shielded syringe for withdrawing and injecting the preparation.

Radiation Dosimetry

The estimated absorbed radiation doses^2from an intravenous injection of 185 megabecquerels (5 millicuries) of Gallium Citrate Ga 67 are shown in Table 4.

Table 4. Absorbed Radiation Doses
Tissue | mGy/ 185MBq | rads/ 5mCi
Whole Body Skeleton Liver Bone Marrow Spleen Kidney Ovaries Testes Gastrointestinal Tract Stomach Small Intestine Upper Large Intestine Lower Large Intestine | 13.0 22.0 23.0 29.0 26.5 20.5 14.0 12.0 11.0 18.0 28.0 45.0 | 1.30 2.20 2.30 2.90 2.65 2.05 1.40 1.20 1.10 1.80 2.80 4.50

^2 MIRD Dose Estimate Report No. 2, J. Nucl. Med. 14; 755-6 (1973).

HOW SUPPLIED

Catalog Number 180.

Gallium Citrate Ga 67 Injection is supplied sterile and non-pyrogenic for intravenous use. Each milliliter contains 74 megabecquerels (2 millicuries) of gallium Ga-67 on the calibration date, as a complex formed from 8.3 nanograms gallium chloride Ga-67, 1.9 milligrams of sodium citrate dihydrate, 7.8 milligrams of sodium chloride, and 0.9 percent benzyl alcohol (v/v) as a preservative. The pH is adjusted to between 5.5 to 8.0 with hydrochloric acid and/or sodium hydroxide solution.

Gallium Citrate Ga 67 Injection is available in vials containing the following amounts on the calibration date.

Catalog No.

N180G0 222 megabecquerels (6 mCi)

NDC 69945-180-06

N180M0 444 megabecquerels (12 mCi)

NDC 69945-180-12

Storage and Handling

The contents of the vial are radioactive, and adequate shielding and handling precautions must be maintained. Store at controlled room temperature 20° to 25°C
(68° to 77°F) [see USP].

Storage and disposal of Gallium Citrate Ga 67 Injection should be controlled in a manner that is in compliance with the appropriate regulations of the government agency authorized to license the use of this radionuclide.

©2022 Curium US LLC. CuriumTMand the Curium logo are trademarks of a Curium company.

Manufactured by:
Curium US LLC
Maryland Heights, MO 63043

Made in USA

A180I0

R07/2022

PRINCIPAL DISPLAY PANEL

Gallium Citrate Ga 67 Injection

DIAGNOSTIC Sterile, Non-Pyrogenic Solution
For Intravenous Administration

Store at Controlled Room Temperature 20° to 25°C (68° to 77°F).

Each milliliter contains 74 MBq (2 mCi) Gallium Citrate Ga 67 (essentially carrier free) at date and time of calibration, as a complex formed from
8.3 ng gallium chloride Ga 67, 1.9 mg sodium citrate dihydrate, 7.8 mg sodium chloride, and 0.9% (v/v), benzyl alcohol as a preservative. Sodium hydroxide or hydrochloric acid are added for pH adjustment. The pH is between 5.5 and 8.0.

For information on dosage, administration and indications see package insert.

Rx only

WARNING: Radioactive drugs must be handled only by qualifed personnel in conformity with regulations of the U.S. Nuclear Regulatory commission or state regulatory agencies where applicable. Bottle containing drug should be kept in this container or within heavier shield.

Total Act. MBq (mCi)

As of 12 Noon CT As of

Volume mL
Conc. MBq/mL
(mCi/mL)

Sp. Act. Essentially Carrier-Free
Exp.
Lot

Gallium Citrate
Ga 67 Injection
DIAGNOSTIC

Manufactured by:
Curium US LLC
Maryland Heights, MO 63043
Made in USA

CURIUMTM